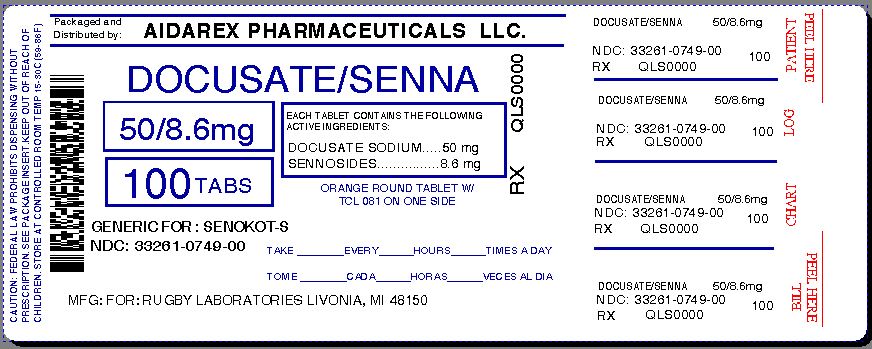 DRUG LABEL: SENEXON-S
NDC: 33261-749 | Form: TABLET, COATED
Manufacturer: Aidarex Pharmaceuticals LLC
Category: otc | Type: HUMAN OTC DRUG LABEL
Date: 20131230

ACTIVE INGREDIENTS: DOCUSATE SODIUM 50 mg/1 1; SENNOSIDES A AND B 8.6 mg/1 1
INACTIVE INGREDIENTS: CARNAUBA WAX; SILICON DIOXIDE; CROSCARMELLOSE SODIUM; D&C YELLOW NO. 10; CALCIUM PHOSPHATE, DIBASIC, DIHYDRATE; FD&C YELLOW NO. 6; HYPROMELLOSE 2910 (6 MPA.S); MAGNESIUM STEARATE; CELLULOSE, MICROCRYSTALLINE; POLYETHYLENE GLYCOLS; SODIUM BENZOATE; STEARIC ACID; TITANIUM DIOXIDE

DOCUSATE SOD SENNA 50 8 6MG FOR RUGBY

Active ingredients (in each tablet)

Docusate sodium 50 mg

Sennosides 8.6 mg

ASK A DOCTOR BEFORE USE IF YOU HAVE A SUDDEN CHANGE IN BOWEL HABITS THAT LASTS OVER TWO WEEKS

Ask a doctor or pharmacist berfore use if you are taking any other drug. Laxatives may affect how other drugs work.

Do not use if your are taking mineral oil; for longer than one week; when abdominal pain, nausea or vomiting are present

Keep out of reach of children. In case of overdose, get medical help or contact a Poison Control Center right away.

PREGNANCY OR BREAST FEEDING

If pregnant or breast-feeding, ask a health professional before use.

PURPOSE

Uses: relieves occasional constipation; generally produces bowel movement in 6-12 hours.

QUESTIONS

call 1 800 645-2158 9 am - 5 pm Monday - Friday

Stop use and ask a doctor if: you have rectal bleeding; you fail to have a bowel movement after use of this product. These may indicate a serious condition.

Inactive ingredients

carnauba wax, colloidal silicon dioxide, croscarmellose sodium

D-C yellow #10 aluminum lake, dibasic calcium phosphate

dihydrate, FD-C yellow #6 aluminum lake, hypromellose,

magnesium stearate, microcrystalline cellulose, polyethylene

glycol, sodium benzoate, stearic acide, Titanium dioxide

WHEN USING

Directions take preferably at bedtime or as directed by a doctor

If you do not have a comfortable bowel movement by the second day, increase dose by one tablet (do not exceed maxiumum dosage)

Dosage and Administration

Adults and children 12 years and over - 2 tablets once a day - maximum dosage - 4 tablets twice a day

children 6 to under 12 years - 1 tablet once a day maximum dosage - 2 tablets twice a day

children 2 to under 6 years - 1/2 tablet once a day - maximum dosage- 1 tablet twice a day

children uner 2 years - ask a doctor

INDICATIONS AND USAGE

RELIEVES OCCASIONAL CONSTIPATION

GENERALLY PRODUCES BOWEL MOVEMENT IN 6-12 HOURS

PACKAGE LABEL

Repackaged By :
Aidarex Pharmaceuticals LLC,
Corona, CA 92880